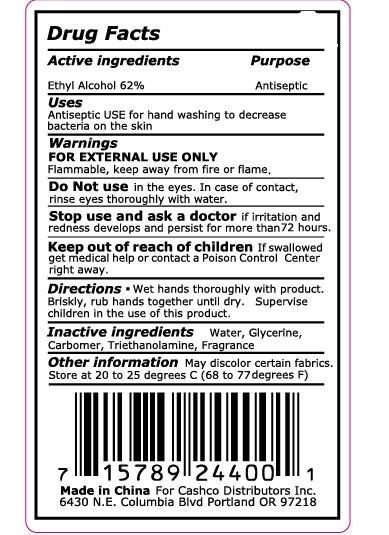 DRUG LABEL: Good to Go Hand Sanitizer
NDC: 42086-101 | Form: LIQUID
Manufacturer: Jiangsu Gold Worldworks Household Chemicals Co., Ltd.
Category: otc | Type: HUMAN OTC DRUG LABEL
Date: 20180405

ACTIVE INGREDIENTS: ALCOHOL 62 mL/100 mL
INACTIVE INGREDIENTS: WATER 36.7 mL/100 mL; CARBOMER COPOLYMER TYPE A; TROLAMINE; GLYCERIN

Drug Fact

Active Ingredient

Ethyl Alcohol 62%

Purpose

Antiseptic

Uses

Antiseptic Use for hand washing to decrease bacteria on the skin

WARNINGS

For external use only-hands

Flammable: Keep away from heat and flame

When using this product: Keep out of eyes. In case of contact with eyes, flush thoroughly with water.

Stop use and ask a doctor if skin irritation develops and persist for more than 72 hours

Keep out of reach of children. In case of accidental ingestion, get medical help or contact a Poison Control Center immediately

Directions

- Wet hands thoroughly with product. Briskly, rub hands together until dry. Supervise children in the use of this product.

Other Information:

- May discolor some fabrics
- Store at 20-25 degree C (68-77 degree F)

Inactive Ingredient:

Deionized Water, Glycerin, Triethanolamine, Carbomer, Fragrance.